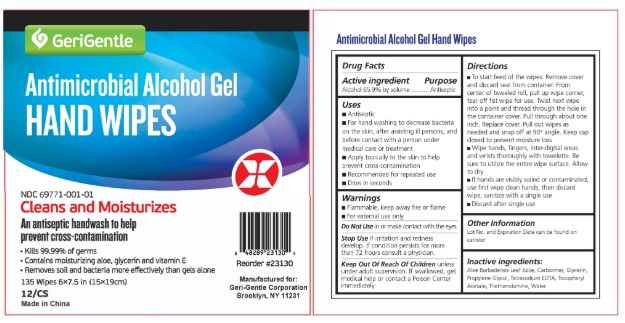 DRUG LABEL: Instant Hand Sanitizeing Wipe
NDC: 79913-201 | Form: CLOTH
Manufacturer: SHANDONG HENGFA HYGIENIC PRODUCTS CO., LTD.
Category: otc | Type: HUMAN OTC DRUG LABEL
Date: 20260108

ACTIVE INGREDIENTS: ALCOHOL 1 mL/1 1
INACTIVE INGREDIENTS: HYDROGEN PEROXIDE; WATER

Instant Hand Sanitizeing Wipe

Instant Hand Sanitizeing Wipe

Active Ingredient(s)

Alcohol 1mL/pcs. Purpose: Antiseptic

Purpose

Antiseptic

Use

To help reduce bacteria that potentially can cause disease. For use when soap and water are not available.

Warnings

For external use only. Flammable. Keep away from heat or flame

Do not use

- in children less than 2 months of age
- on open skin wounds

When using this product keep out of eyes, ears, and mouth. In case of contact with eyes, rinse eyes thoroughly with water.
Stop use and ask a doctor if irritation or rash occurs. These may be signs of a serious condition.
Keep out of reach of children. If swallowed, get medical help or contact a Poison Control Center right away.

Stop use and ask a doctor if irritation or rash occurs. These may be signs of a serious condition.

Keep out of reach of children. If swallowed, get medical help or contact a Poison Control Center right away.

Directions

- Wipe the surface of the skin

Other information

- Store between 15-30C (59-86F)
- Avoid freezing and excessive heat above 40C (104F)

Inactive ingredients

WATER
HYDROGEN PEROXIDE